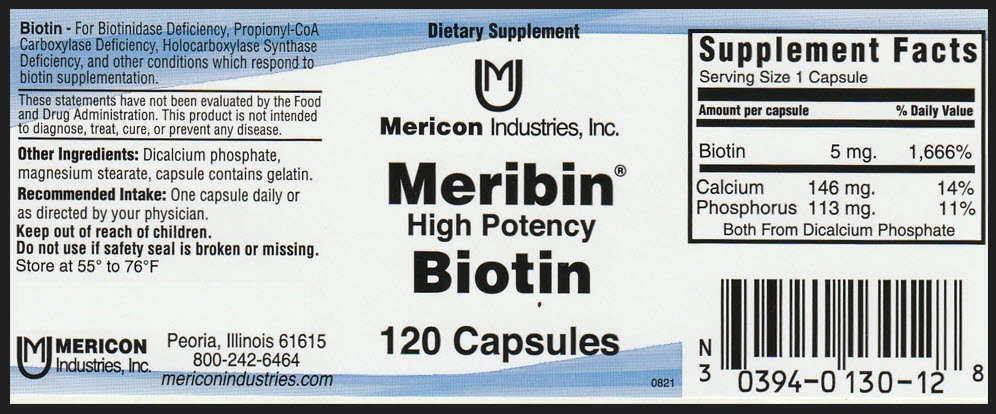 DRUG LABEL: Meribin Biotin
NDC: 0394-0130 | Form: CAPSULE
Manufacturer: Mericon Industries
Category: other | Type: DIETARY SUPPLEMENT
Date: 20250115

ACTIVE INGREDIENTS: BIOTIN 5 mg/1 1; CALCIUM 146 mg/1 1; PHOSPHORUS 113 mg/1 1
INACTIVE INGREDIENTS: MAGNESIUM STEARATE; GELATIN, UNSPECIFIED

Meribin® Biotin

Bioton

For Biotinidase Deficiency, Propionyl-CoA Carboxylase Deficiency, Holocarboxylase Synthase Deficiency, and other conditions which respond to biotin supplementation.

HEALTH CLAIM

These statements have not been evaluated by the Food and Drug Administration. This product is not intended to diagnose, treat, cure, or prevent any disease.

Other Ingredients

Dicalcium phosphate, magnesium stearate, capsule contains gelatin.

Recommended Intake

One capsule daily or as directed by your physician.

Keep out of reach of children.
Do not use if safety seal is broken or missing.

HEALTH CLAIM

Store at 55° to 76° F

HEALTH CLAIM

MERICON
Industries, Inc.

Peoria, Illinois 61615
800-242-6464
mericonindustries.com

STATEMENT OF IDENTITY

Supplement Facts
Serving Size 1 Capsule
Amount per capsule |  |  | % Daily Value
Biotin | 5 mg. |  | 1,666%
Calcium | 146 mg. |  | 14%
Phosphorus | 113 mg. |  | 11%
Both From Dicalcium Phosphate

PRINCIPAL DISPLAY PANEL -120 Capsule Bottle Label

Dietary Supplement

Mericon Industries, Inc.

Meribin®
High Potency
Biotin

120 Capsules

0821